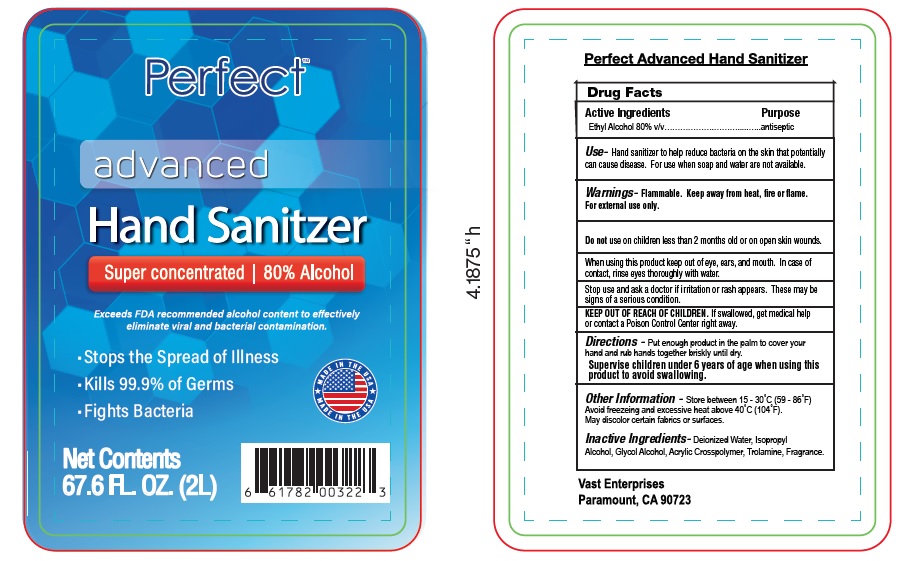 DRUG LABEL: Perfect advanced hand sanitizer
NDC: 73919-001 | Form: LIQUID
Manufacturer: VAST ENTERPRISES
Category: otc | Type: HUMAN OTC DRUG LABEL
Date: 20200326

ACTIVE INGREDIENTS: ALCOHOL 80 mL/100 mL
INACTIVE INGREDIENTS: WATER; ISOPROPYL ALCOHOL; CARBOMER HOMOPOLYMER TYPE C (ALLYL PENTAERYTHRITOL CROSSLINKED); TROLAMINE; GLYCERIN

PERFECT ADVANCED HAND SANITIZER

Active ingredient

Ethyl alcohol 80% v/v

Purpose

Antiseptic

Uses

Hand sanitizer to help reduce bacteria on the skin that potentially can cause disease. For use when soap and water are not available.

Warnings

Flammable, keep away from fire or flame

For external use only

Do not use onchildren less than 2 months old or on open skin wounds.

When using this product

keep out of eye. In case of contact rinse eyes thoroughly with water

Stop use and ask doctor if

irritation or rash appears. These may be signs of a serious condition.

Keep out of reach of children.

If swallowed, get medical help right away or contact a Poison Control Center immediately.

Directions

Put enough product in the palm to cover your hand and rub hands together briskly until dry.

Supervise children under 6 years of age when using this product to avoid swallowing.

Other information

Store between 15 - 30˚C (59 - 86˚F)
Avoid freezeing and excessive heat above 40˚C (104˚F).
May discolor certain fabrics or surfaces.

Inactive ingredient

Deionized Water, Isopropyl Alcohol, Glycol Alcohol, Acrylic Crosspolymer, Trolamine, Fragrance.